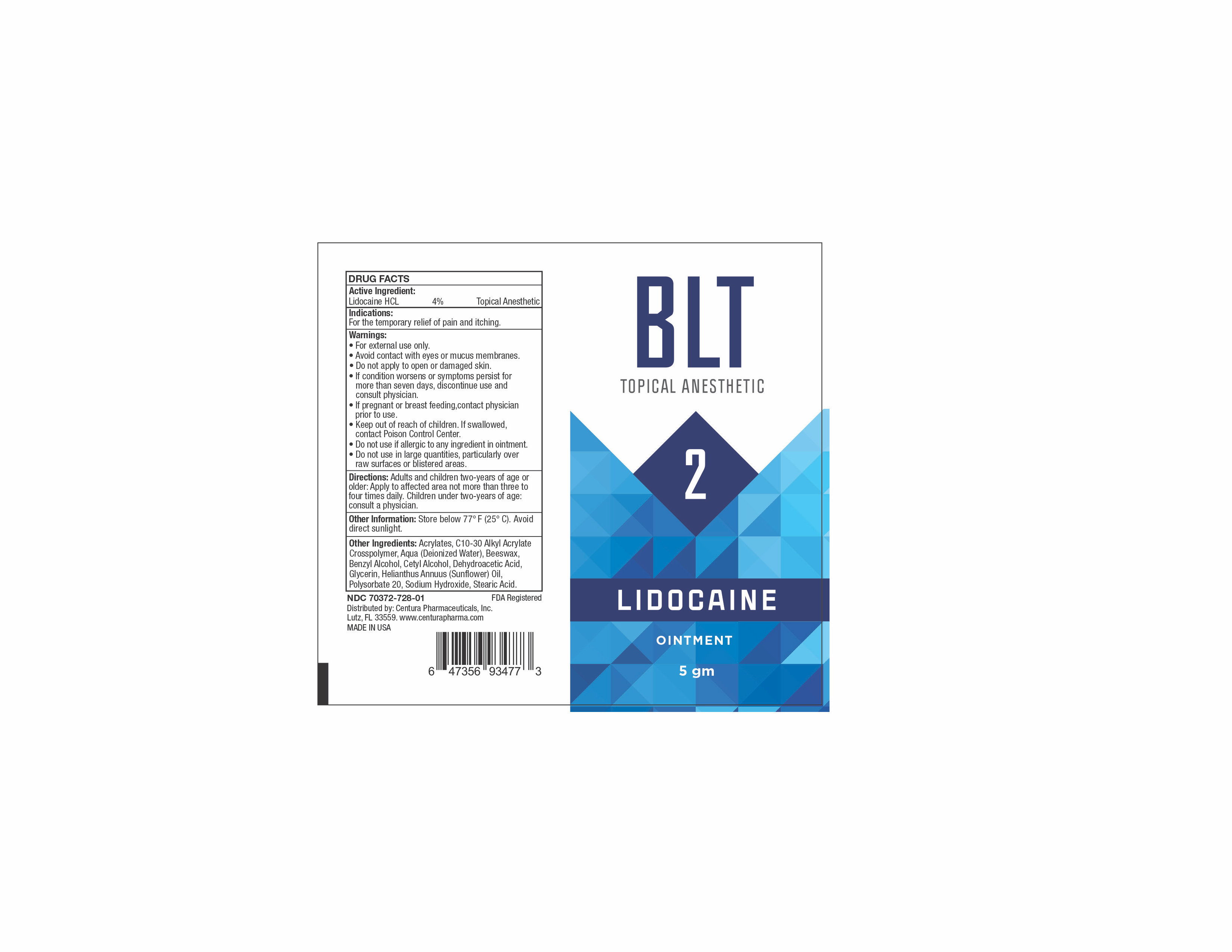 DRUG LABEL: BLT 2
NDC: 70372-728 | Form: OINTMENT
Manufacturer: CENTURA PHARMACEUTICALS INC
Category: otc | Type: HUMAN OTC DRUG LABEL
Date: 20260112

ACTIVE INGREDIENTS: LIDOCAINE HYDROCHLORIDE 4 g/100 g
INACTIVE INGREDIENTS: GLYCERIN; SUNFLOWER OIL; CARBOMER INTERPOLYMER TYPE A (ALLYL SUCROSE CROSSLINKED); BENZYL ALCOHOL; POLYSORBATE 20; CETYL ALCOHOL; YELLOW WAX; STEARIC ACID; DEHYDROACETIC ACID; SODIUM HYDROXIDE; WATER

ACTIVE INGREDIENT

Lidocaine HCL 4%

PURPOSE

Topical Anesthetic

USES

For the temporary relief of pain and itching.

WARNINGS

• For external use only.
• Avoid contact with eyes or mucus membranes.
• Do not apply to open or damaged skin.
• If condition worsens or symptoms persist for
more than seven days, discontinue use and
consult physician.
• If pregnant or breast feeding,contact physician
prior to use.
• Keep out of reach of children. If swallowed,
contact Poison Control Center.
• Do not use if allergic to any ingredient in ointment.
• Do not use in large quantities, particularly over
raw surfaces or blistered areas.

DIRECTIONS

Adults and children two-years of age or
older: Apply to affected area not more than three to
four times daily. Children under two-years of age:
consult a physician.

OTHER INFORMATION

Store below 77° F (25° C). Avoid
direct sunlight.

INACTIVE INGREDIENTS

Acrylates, C10-30 Alkyl Acrylate Crosspolymer, Aqua (Deionized Water), Beeswax, Benzyl Alcohol, Cetyl Alcohol, Dehydroacetic Acid, Glycerin, Helianthus Anuus (Sunflower) Oil, Polysorbate 20, Sodium Hydroxide, Stearic Acid.